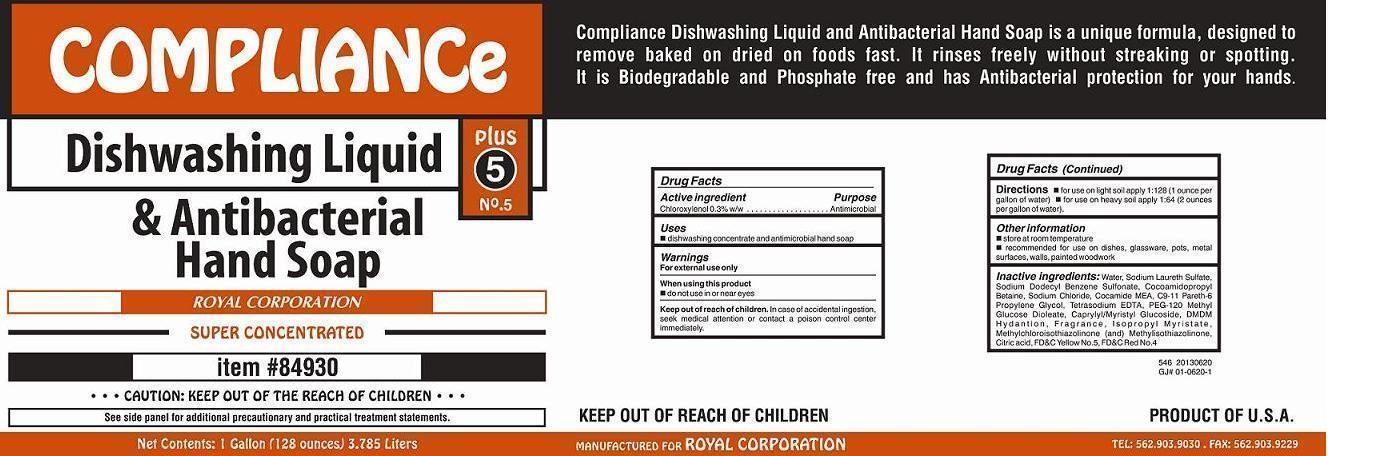 DRUG LABEL: COMPLIANCE DISHWASHING LIQUID
NDC: 59723-546 | Form: SOAP
Manufacturer: ROYAL PAPER CORPORATION
Category: otc | Type: HUMAN OTC DRUG LABEL
Date: 20130926

ACTIVE INGREDIENTS: CHLOROXYLENOL 3 g/1000 mL
INACTIVE INGREDIENTS: WATER; SODIUM DODECYLBENZENESULFONATE; DECYL GLUCOSIDE; LAURYL GLUCOSIDE; COCO MONOETHANOLAMIDE; C9-11 PARETH-6; SODIUM LAURETH SULFATE; PROPYLENE GLYCOL; ISOPROPYL MYRISTATE; METHYLCHLOROISOTHIAZOLINONE; METHYLISOTHIAZOLINONE; COCAMIDOPROPYL BETAINE; DMDM HYDANTOIN; PEG-120 METHYL GLUCOSE DIOLEATE; EDETATE SODIUM; CITRIC ACID MONOHYDRATE; SODIUM CHLORIDE

Active ingredient

Chloroxylenol 0.3% w/w

Purpose

Antimicrobial

Keep out of reach of children

In case of accidental ingestion, seek medical attention or contact a poison control center immediately.

Uses

- dishwashing concentrate and antimicrobial hand soap

Warnings

For external use only

When using this product

- do not use in or near eyes

Directions

 for use on light soil soil apply 1:128 (1 ounce per gallon of water)  for use on heavy soil apply 1:64 (2 ounces per gallon of water).

Other information

 store at room temperature

 recommended for use on dishes, glassware, pots, metal surfaces, walls, painted woodwork

Inactive ingredients:

Water, Sodium Laureth Sulfate, Sodium Dodecyl Benzene Sulfonate, Cocoamidopropyl Betaine, Sodium Chloride, Cocamide MEA, C9-11 Pareth-6, Propylene Glycol, Tetrasodium EDTA, PEG-120 Methyl Glucose Dioleate, Caprylyl/Myristyl Glucoside, DMDM H y d a n t i o n , F r a g r a n c e , I s o p r o p y l M y r i s t a t e, Methylchloroisothiazolinone (and) Methylisothiazolinone, Citric acid, FD&C Yellow No.5, FD&C Red No.4